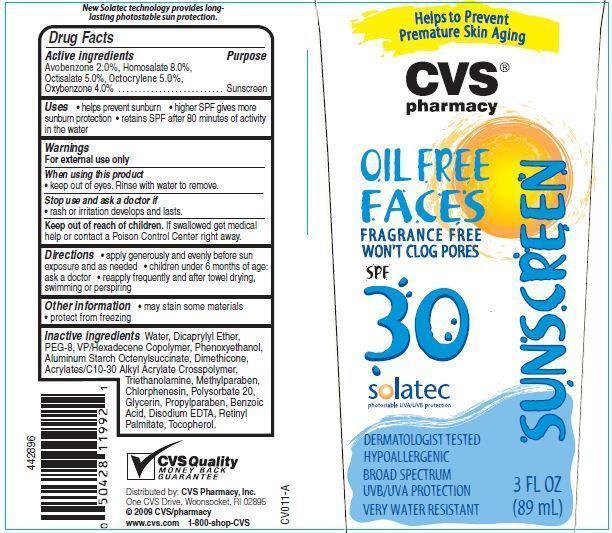 DRUG LABEL: CVS Pharmacy Oil Free Faces SPF 30
NDC: 59779-023 | Form: LOTION
Manufacturer: CVS Pharmacy
Category: otc | Type: HUMAN OTC DRUG LABEL
Date: 20121213

ACTIVE INGREDIENTS: AVOBENZONE 2 g/100 g; HOMOSALATE 8 g/100 g; OCTISALATE 5 g/100 g; OCTOCRYLENE 5 g/100 g; OXYBENZONE 4 g/100 g
INACTIVE INGREDIENTS: WATER; DICAPRYLYL ETHER; PHENOXYETHANOL; ALUMINUM STARCH OCTENYLSUCCINATE; DIMETHICONE; TROLAMINE; METHYLPARABEN; CHLORPHENESIN; POLYSORBATE 20; GLYCERIN; PROPYLPARABEN; BENZOIC ACID; EDETATE DISODIUM; VITAMIN A PALMITATE; TOCOPHEROL

Drug Facts

Active ingredients

Avobenzone 2.0%
Homosalate 8.0%
Octisalate 5.0%
Octocrylene 5.0%
Oxybenzone 4.0%

Purpose

Sunscreen

Uses

- helps prevent sunburn
- higher SPF gives more sunburn protection
- retains SPF after 80 minutes of activity in water

Warnings

For external use only

When using this product

- keep out of eyes. Rinse with water to remove.

Stop use and ask a doctor if

- rash or irritation develops and lasts.

Keep out of the reach of children.
If swallowed get medical help or contact a Poison Control Center right away.

Directions

- apply generously and evenly before sun exposure and as needed
- children under 6 months of age: ask a doctor
- reapply frequently and after towel drying, swimming or perspiring

Other information

- may stain some materials
- protect from freezing

Inactive ingredients

Water, Dicaprylyl Ether, PEG-8, VP/Hexadecene Copolymer, Aluminum Starch Octenylsuccinate, Dimethicone, Acrylates/C10-30 Alkyl Acrylate Crosspolymer, Triethanolamine, Polysorbate 20, Glycerin, Benzoic Acid, Disodium EDTA, Retinyl Palmitate, Tocopherol, Phenoxyethanol, Methylparaben, Chlorphenesin, Propylparaben.

Principal Display Panel

Helps to Prevent Premature Skin Aging
CVS
pharmacy
SUSCREEN
OIL FREE FACES
FRAGANCE FREE
WON'T CLOG PORES
SPF 30
solatec
photostable UVA/UVB protection
DERMATOLOGIST TESTED
HYPOALLERGENIC
BROAD SPECTRUM
UVA/UVB PROTECTION
VERY WATER RESISTANT
3 FL OZ(89 mL)